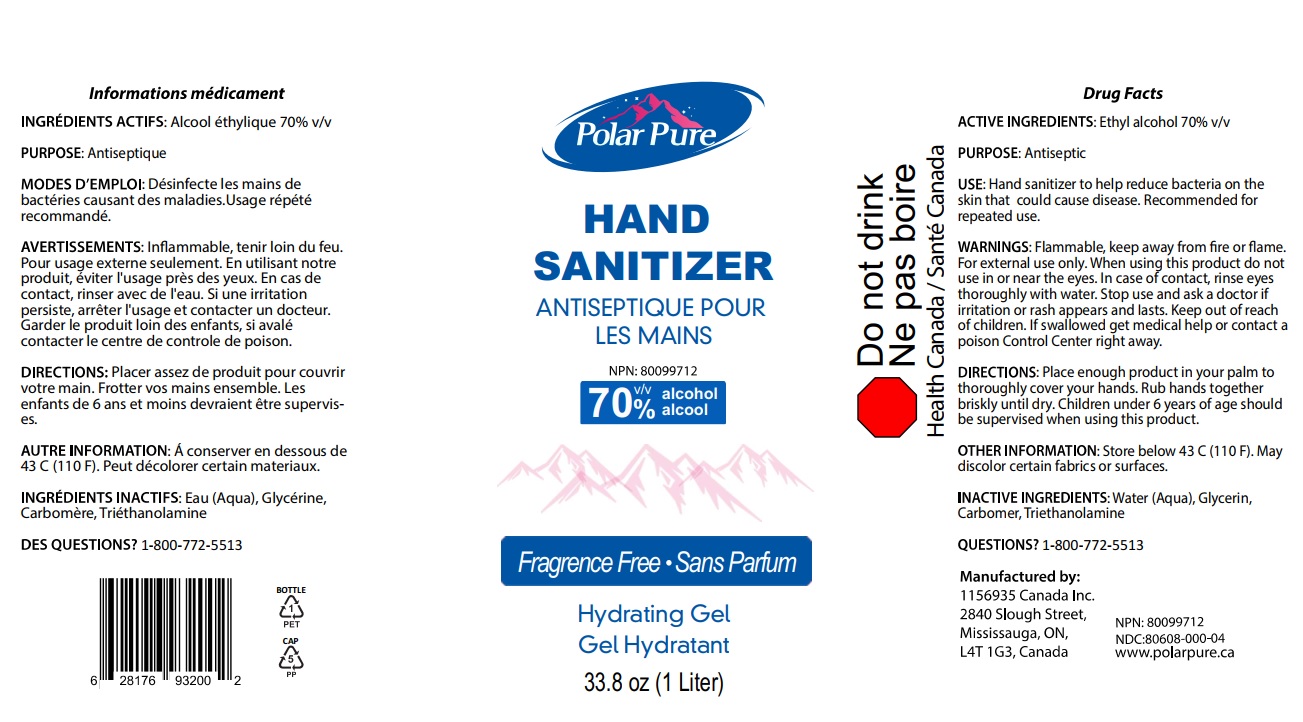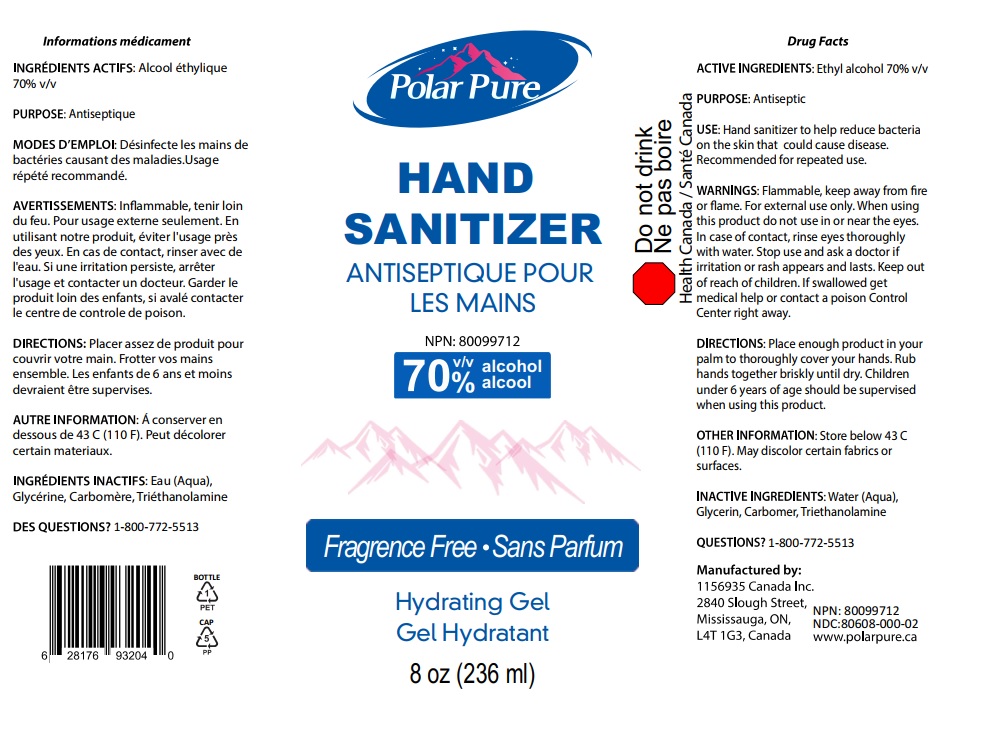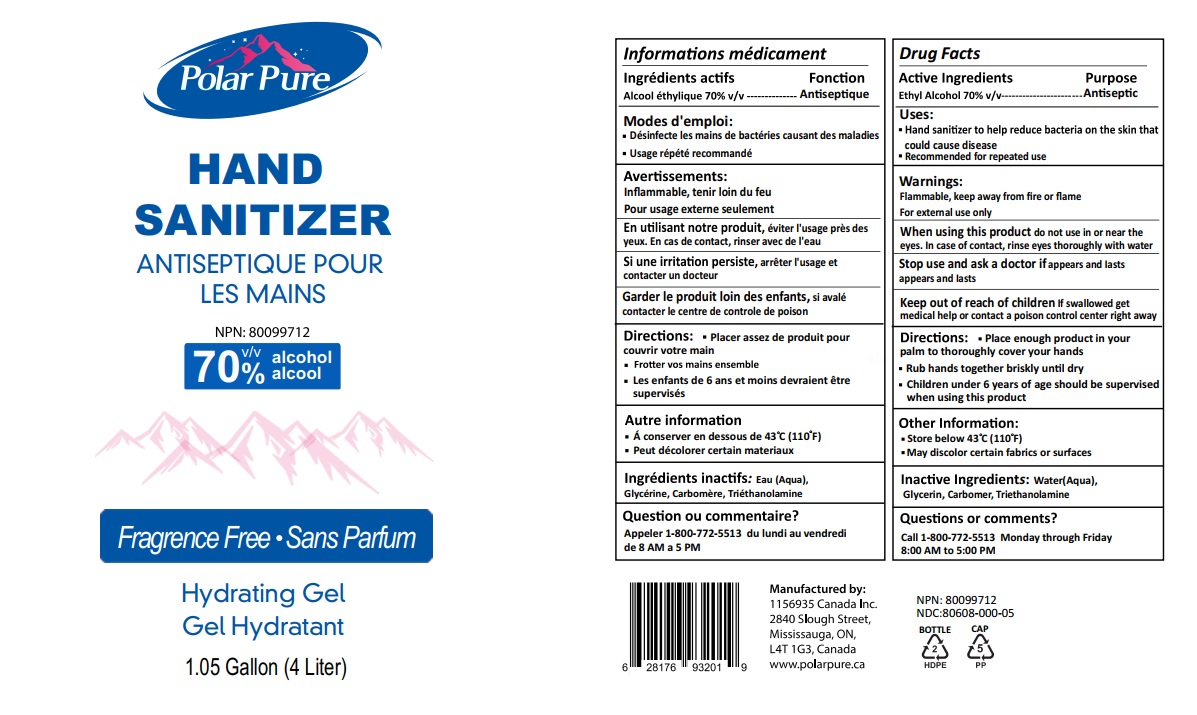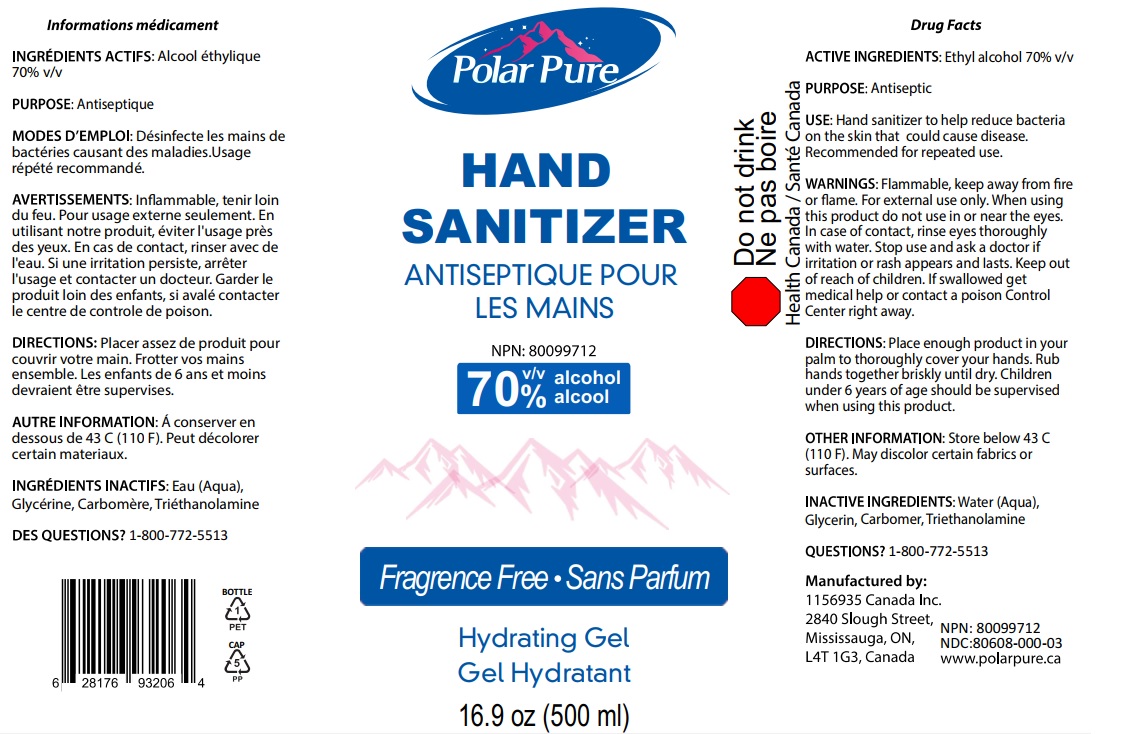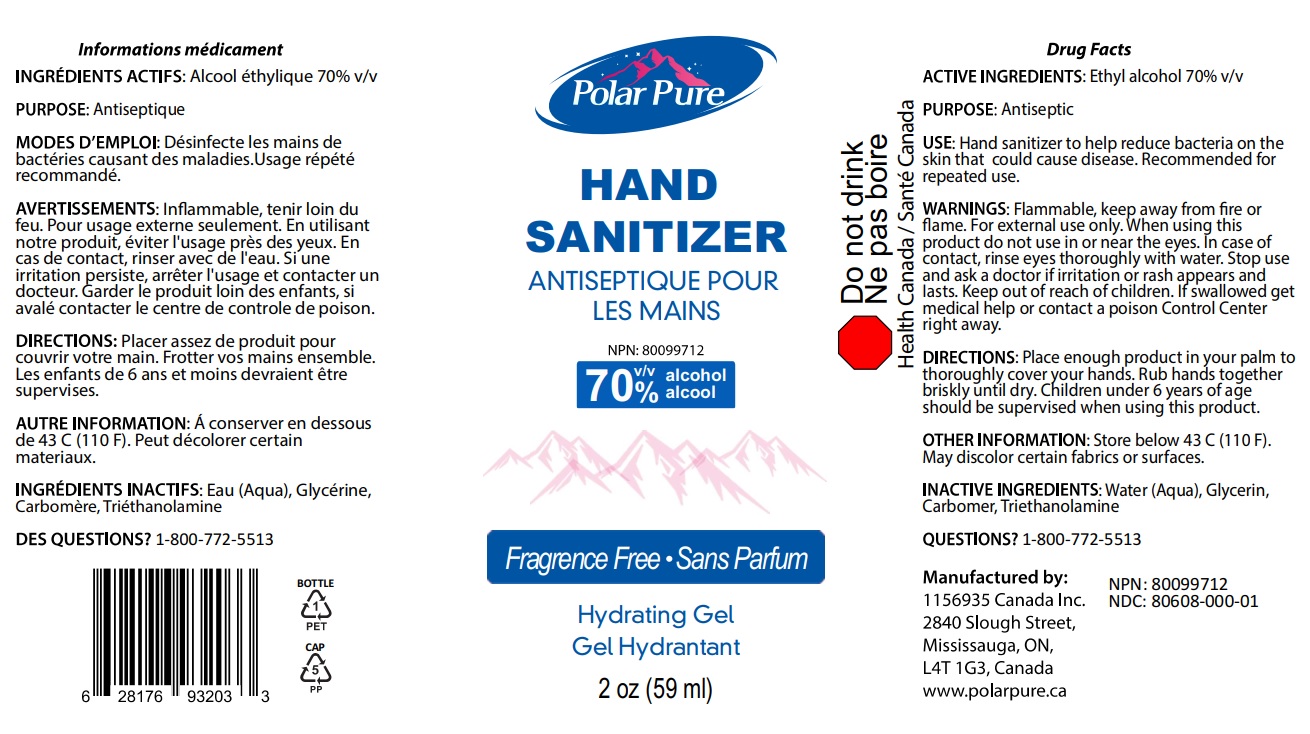 DRUG LABEL: Polar Pure Hand Sanitizer
NDC: 80608-000 | Form: LIQUID
Manufacturer: 11569635 Canada Inc
Category: otc | Type: HUMAN OTC DRUG LABEL
Date: 20201012

ACTIVE INGREDIENTS: ALCOHOL 0.7 mL/1 mL
INACTIVE INGREDIENTS: WATER; GLYCERIN; CARBOMER HOMOPOLYMER, UNSPECIFIED TYPE; TROLAMINE

Polar Pure Hand Sanitizer

ACTIVE INGREDIENTS:

Ethyl alcohol 70% v/v

PURPOSE:

Antimicrobial

USE:

Hand sanitizer to help reduce bacteria on the skin that could cause disease.Recommended for repeated use.

WARNINGS:

Flammable, keep away from fire or flame. For external use only.

When using this product

do not use in or near the eyes. In case of contact, rinse eyes thoroughly with water.

Stop use and ask a doctor

if irritation or rash appears and lasts.

Keep out of reach of children,

if swallowed get medical help or contact a poison control center right away

DIRECTIONS:

Place enough product in your palm to thoroughly cover your hands. Rub hands briskly until dry. Children under 6 years of age should be supervised when using this product.

OTHER INFORMATION:

Store below 43 C (110 F). May discolor certain fabrics or surfaces.

INACTIVE INGREDIENTS:

Water (Aqua), Glycerin, Carbomer, Triethanolamine

QUESTIONS?

1-800-772-5513